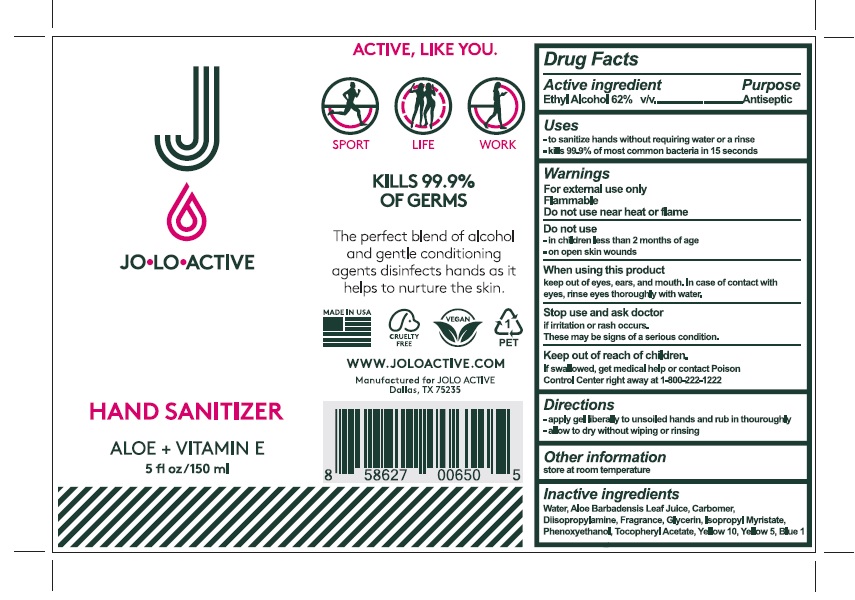 DRUG LABEL: JOLO Active
NDC: 79989-001 | Form: GEL
Manufacturer: FUSION ACCELERATE, LLC
Category: otc | Type: HUMAN OTC DRUG LABEL
Date: 20200911

ACTIVE INGREDIENTS: ALCOHOL 62 mL/100 mL
INACTIVE INGREDIENTS: WATER; ALOE VERA LEAF; CARBOMER HOMOPOLYMER, UNSPECIFIED TYPE; DIISOPROPYLAMINE; GLYCERIN; ISOPROPYL MYRISTATE; PHENOXYETHANOL; .ALPHA.-TOCOPHEROL ACETATE; D&C YELLOW NO. 10; FD&C YELLOW NO. 5; FD&C BLUE NO. 1

Active ingredient

Alcohol 62% v/v

Purpose

Antiseptic

Use

To sanitize hands without requiring water or a rinse – Kills 99.9% of most common bacteria in 15 seconds

Warnings

For external use only

Flammable

Do not use near heat or flame

Do not use

In children less than 2 months of age

On open skin wounds

When using this product keep out of eyes, ears and mouth, In case of contact with eyes, rinse eyes throughly with water.

Stop use and ask a doctor

if irritation or rash occurs.

They may be signs of a serious condition.
Keep out of reach of children. If swallowed, get medical help or contact a Poison Control Center right away atv 1-800-222-1222

Directions

Apply gel liberally to unsoiled hands and rub in thoroughly

Allow to dry without wiping or rinsing

Other information

- Store at room temperature.

Inactive ingredients

Water, Aloe barbadensis Leaf Juice, Carbomer, Diisopropylamine, Glycerin, Isopropyl Myristate, Fragrance, Phenoxyethanol, Tocopheryl Acetate, Yellow 10, Yellow 5, Blue 1.